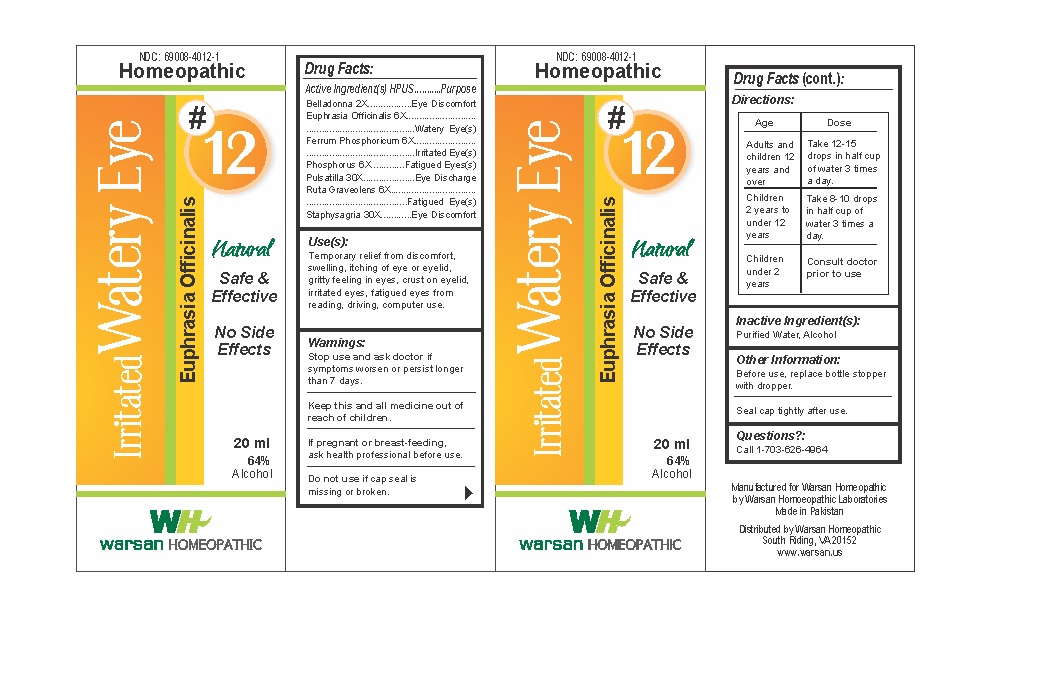 DRUG LABEL: Combination Remedy 12 - Irritated Watery Eye
NDC: 69008-4012 | Form: SOLUTION/ DROPS
Manufacturer: Warsan Homoeopathic Laboratories
Category: homeopathic | Type: HUMAN OTC DRUG LABEL
Date: 20171225

ACTIVE INGREDIENTS: FERRUM PHOSPHORICUM 6 [hp_X]/1 mL; PHOSPHORUS 6 [hp_X]/1 mL; ATROPA BELLADONNA 2 [hp_X]/1 mL; RUTA GRAVEOLENS FLOWERING TOP 6 [hp_X]/1 mL; DELPHINIUM STAPHISAGRIA SEED 30 [hp_X]/1 mL; EUPHRASIA STRICTA 6 [hp_X]/1 mL; PULSATILLA VULGARIS 30 [hp_X]/1 mL
INACTIVE INGREDIENTS: ALCOHOL; WATER

Stop use and ask doctor if symptoms worsen or persist longer than 7 days.

If pregnant or breast-feeding, ask health professional before use.

Do not use if tamper evident seal is missing or broken.

Keep out of reach of children.

ACTIVE INGREDIENT

Belladonna 2X

Euphrasia Officinalis 6X

Ferrum Phosphoricum 6X

Phosphorus 6X

Pulsatilla 30X

Ruta Graveolens 6X

Staphysagria 30X

PURPOSE

Temporary relief from discomfort, swelling, itching of eye or eyelid, gritty feeling in eyes, crust on eyelid, irritated eyes, fatigued eyes from reading, driving, computer use.

INACTIVE INGREDIENT

Purified Water

Alcohol

DOSAGE AND ADMINISTRATION

Adults and children 12 years and older: Take 10-15 drops in half cup of water 3 times a day.

Children 2 years to under 12 years: Take 8-10 drops in half cup of water of 3 times a day.

Children under 2 years: Consult doctor prior to use.

INDICATIONS AND USAGE

Temporary relief from discomfort, swelling, itching of eye or eyelid, gritty feeling in eyes, crust on eyelid, irritated eyes, fatigued eyes from reading, driving, computer use.